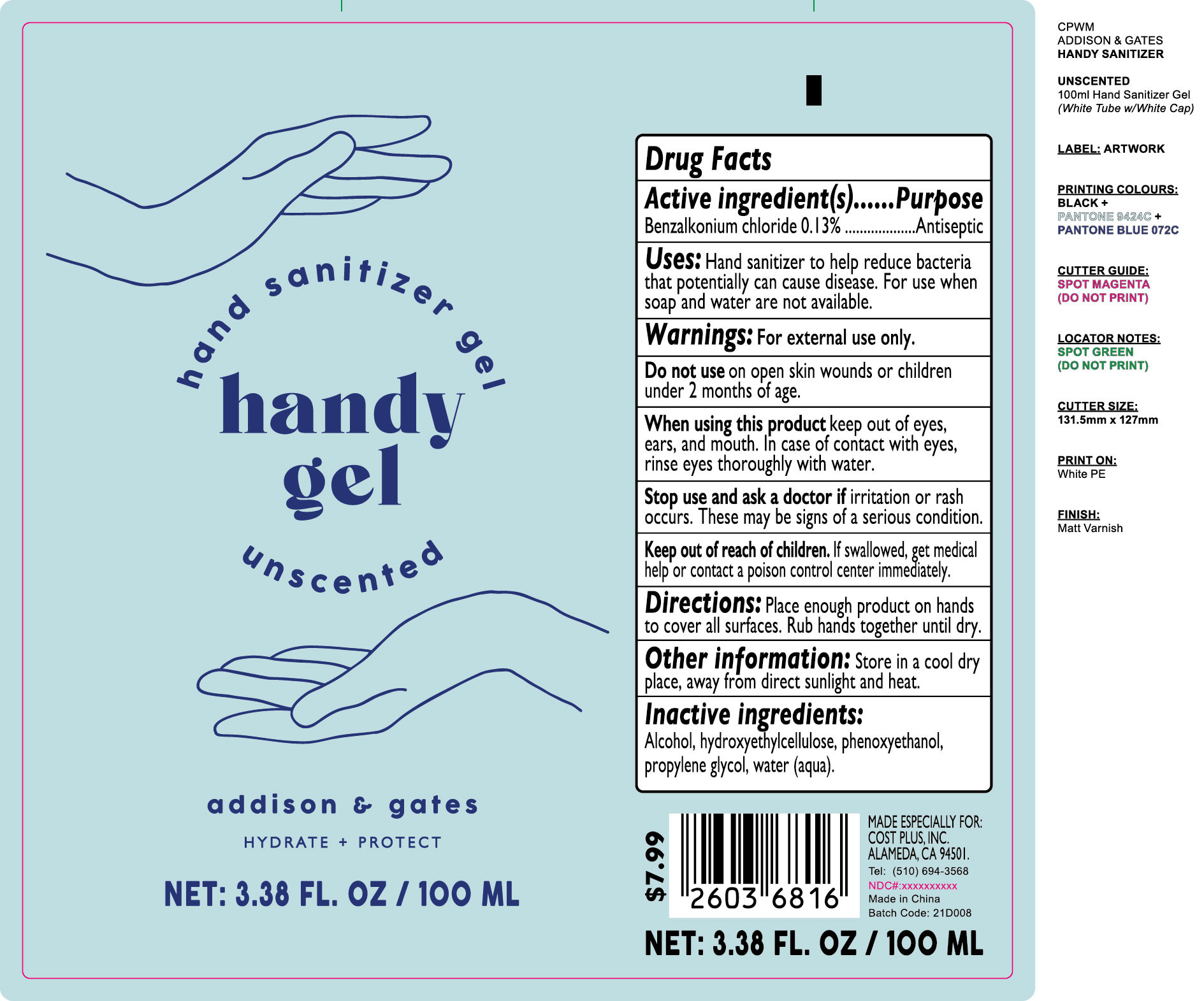 DRUG LABEL: Hand Sanitizer Gel
NDC: 81726-002 | Form: GEL
Manufacturer: The Source Design Collections
Category: otc | Type: HUMAN OTC DRUG LABEL
Date: 20210416

ACTIVE INGREDIENTS: BENZALKONIUM CHLORIDE 0.13 g/100 mL
INACTIVE INGREDIENTS: WATER; HYDROXYETHYL CELLULOSE, UNSPECIFIED; PHENOXYETHANOL; ALCOHOL; PROPYLENE GLYCOL

ACTIVE INGREDIENT

Benzalkonium Chloride 0.13%

PURPOSE

Antiseptic

Uses

Hand sanitizer to help reduce bacteria that potentially can cause disease. For use when soap and water are not available.

INACTIVE INGREDIENT

Water(aqua), propylene glycol, hydroxyethylcellulose, phenoxyethanol, alcohol

Directions

Place enough product on hands to cover all surfaces.Rub hands together until dry.

WARNINGS

For external use only.

Do not use on open skin wounds or children under 2 months of age.

When using this product keep out of eyes,ears, and mouth. ln case of contact with eyes,rinse eyes thoroughly with water.

Stop use and ask a doctor if irritation or rash occurs.These may be signs of a serious condition.

Keep out of reach of children. If swallowed, get medical help or contact a poison control center immediately.

Other information

Store in a cool dry place, away from direct sunlight and heat.